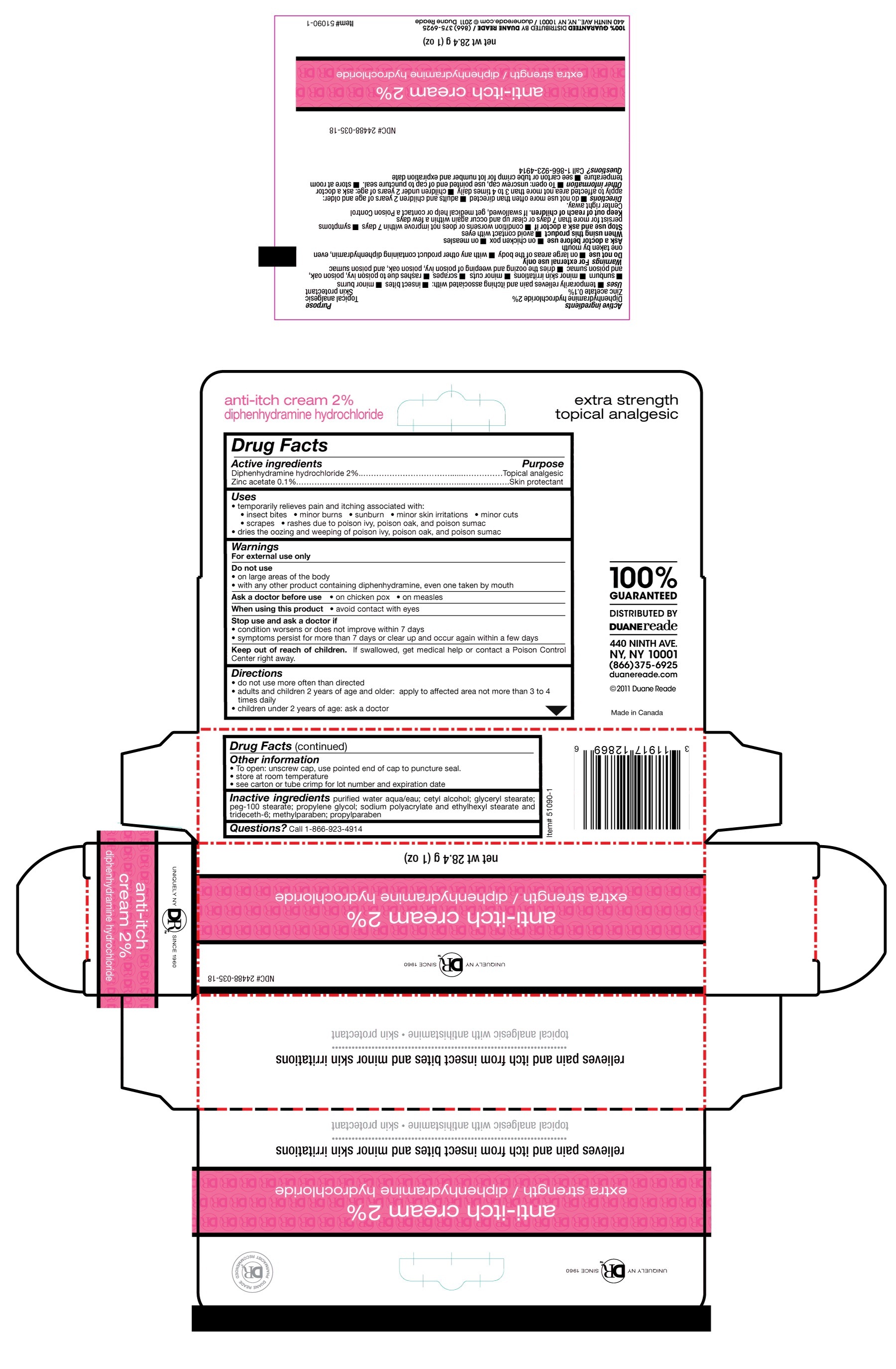 DRUG LABEL: Duane Reade
NDC: 24488-035 | Form: CREAM
Manufacturer: Duane Reade
Category: otc | Type: HUMAN OTC DRUG LABEL
Date: 20110201

ACTIVE INGREDIENTS: DIPHENHYDRAMINE HYDROCHLORIDE .568 g/28.4 g; ZINC ACETATE ANHYDROUS .284 g/28.4 g
INACTIVE INGREDIENTS: WATER; CETYL ALCOHOL; GLYCERYL MONOSTEARATE; POLYOXYL 100 STEARATE; PROPYLENE GLYCOL; SODIUM POLYACRYLATE (8000 MW); ETHYLHEXYL STEARATE; TRIDECETH-6; METHYLPARABEN; PROPYLPARABEN

Drug Facts

Active Ingredient

Diphenhydramine hydrochloride 2%........Topical analgesic
Zinc acetate 0.1%.......Skin protectant

Uses

- temporarily relieves pain and itching associated with:
- insect bites
- minor burns
- sunburn
- minor skin irritations
- minor cuts
- scrapes
- rashes due to poison ivy, poison oak, and poison sumac
- dries the oozing and weeping of poison ivy, poison oak, and poison sumac

Warnings

For external use only

Do not use

- on large areas of the body
- with any other product containing diphenhydramine, even one taken by mouth

Ask a doctor before use

- on chicken pox
- on measles

When using this product

- avoid contact with eyes

Stop use and ask a doctor if

- condition worsens or does not improve within 7 days
- symptoms persist for more than 7 days or clear up and occur again within a few days

Keep out of reach of children.

If swallowed, get medical help or contact a Poison Control Center right away.

Directions

- do not use more often than directed
- adults and children 2 years of age and older: apply to affected area not more than 3 to 4 times daily
- children under 2 years of age: ask a doctor

Other information

- To open: unscrew cap, use pointed end of cap to puncture seal.
- store at room temperature
- see carton or tube crimp for lot number and expiration date

Inactive ingredients

purified water aqua/eau; cetyl alcohol; glyceryl stearate; peg-100 stearate; propylene glycol; sodium polyacrylate and ethylhexyl stearate and trideceth-6; methylparaben; propylparaben

Questions

Call 1-866-923-4914

PACKAGE LABEL

placeholder text